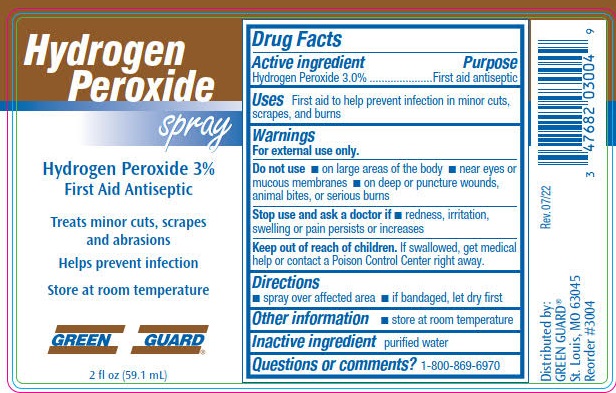 DRUG LABEL: Hydrogen Peroxide
NDC: 47682-304 | Form: LIQUID
Manufacturer: Unifirst First Aid Corporation
Category: otc | Type: HUMAN OTC DRUG LABEL
Date: 20250908

ACTIVE INGREDIENTS: HYDROGEN PEROXIDE 30 mL/1 L
INACTIVE INGREDIENTS: WATER

Green Guard Hydrogen Peroxide Spray

Drug Facts

Active Ingredient

Hydrogen Peroxide 3.0%

Purpose

First aid antiseptic

Uses

First aid to help prevent infection in minor cuts, scrapes and burns

Warnings

For external use only.

Do not use

- on large areas of the body
- near eyes or mucous membranes
- on deep or puncture wounds, animal bites, or serious burns

Stop use and ask a doctor if

- redness, irritation, swelling or pain persists or increases

Keep out of reach of children. If swallowed, get medical help or contact a Poison Control Center right away.

Directions

- spray over affected area
- if bandaged, let dry first

Other information

- store at room temperature

Inactive ingredient

purified water

Questions or Comments? 1-800-869-6970

Green Guard Hydrogen Peroxide Spray Label

Hydrogen Peroxide spray

Hydrogen Peroxide 3%

First Aid antiseptic

Treats minor cuts, scrapes and abrasions

Helps prevent infection

Store at room temperature

GREEN GUARD®

2 fl oz (59.1 mL)